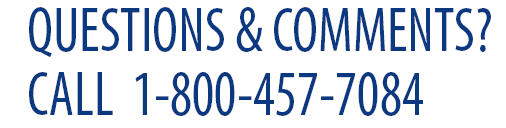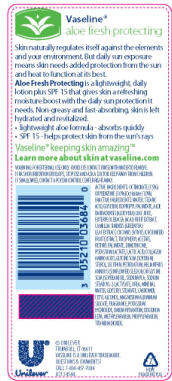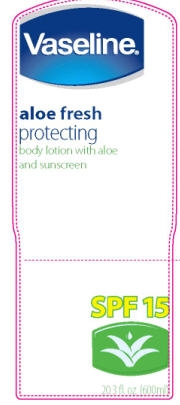 DRUG LABEL: Vaseline Intensive Care
NDC: 64942-1048 | Form: LOTION
Manufacturer: Conopco Inc. d/b/a Unilever
Category: otc | Type: HUMAN OTC DRUG LABEL
Date: 20091104

ACTIVE INGREDIENTS: Octinoxate 7.5 mL/100 mL; Oxybenzone 3.0 mL/100 mL; Octisalate 1.0 mL/100 mL

Drug Facts and PDP for Vaseline Intensive Care Aloe Fresh Protecting Body Lotion SPF 15

WARNINGS

WARNING: FOR EXTERNAL USE ONLY. AVOID EYE CONTACT. RINSE WITH WATER TO REMOVE. IF RASH OR IRRITATION DEVELOPS, STOP USE AND ASK A DOCTOR. KEEP AWAY FROM CHILDREN. IF SWALLOWED, CONTACT A POISON CONTROL CENTER RIGHT AWAY.

ACTIVE INGREDIENTS: OCTINOXATE (7.5%)
OXYBENZONE (3.0%) OCTISALATE (1.0%)

INACTIVE INGREDIENT

Water, Stearic Acid, Glycerin, Isopropyl
Palmitate, Aloe Barbadensis (Aloe Vera) Leaf Juice, Euterpe
Oleracea (Acai) Fruit Extract, Camellia Sinensis (Green Tea)
Leaf Extract, Cucumis Sativus (Cucumber) Fruit Extract, Tocopheryl
Acetate, Retinyl Palmitate, Dimethicone, Potassium Lactate,
Lactic Acid, Collagen Amino Acids, Glycine Soja (Soybean) Sterol,
Lecithin, Petrolatum, Helianthus Annuus (Sunflower) Seed Oil or
Glycine Soja (Soybean) Oil, Sodium PCA, Sodium Stearoyl-2-Lactylate,
Urea, Mineral Water, Glyceryl Stearate, Carbomer, Cetyl Alcohol,
Magnesium Aluminum Silicate, Fragrance, Potassium Hydroxide,
DMDM Hydantoin, Disodium EDTA, Methylparaben, Propylparaben,
Titanium Dioxide.

PACKAGE LABEL

PDP 20.3 oz front

PACKAGE LABEL

PDP 20.3 oz back

Questions section